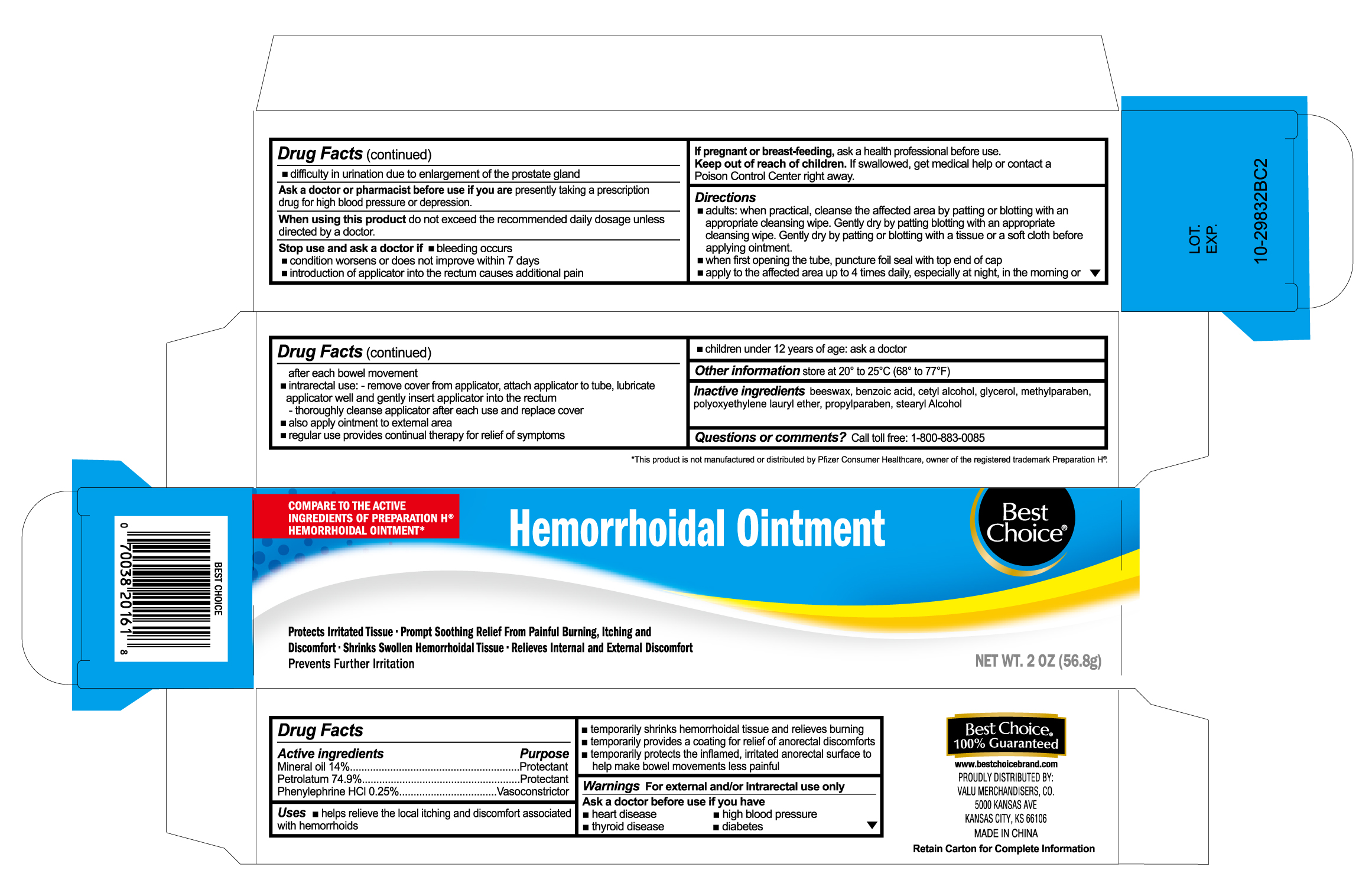 DRUG LABEL: Hemorrhoidal
NDC: 63941-202 | Form: OINTMENT
Manufacturer: Valu Merchandisers, Co.
Category: otc | Type: HUMAN OTC DRUG LABEL
Date: 20230208

ACTIVE INGREDIENTS: MINERAL OIL 14 g/100 g; PETROLATUM 74.9 g/100 g; PHENYLEPHRINE HYDROCHLORIDE 0.25 g/100 g
INACTIVE INGREDIENTS: STEARYL ALCOHOL; GLYCEROL FORMAL; .ALPHA.-SUCCINIMIDYLOXY CARBONYL-.OMEGA.-METHOXY, POLYOXYETHYLENE MW 5000; CETYL ALCOHOL; BENZOIC ACID; PEG-8 BEESWAX; METHYLPARABEN; PROPYLPARABEN

Best Choice Hemorrhoidal Ointment

Uses

- helps relieve the local itching and discomfort associated with hemorrhoids
- temporarily shrinks hemorrhoidal tissue and relieves burning
- temporarily provides a coating for relief of anorectal discomforts
- temporarily protects the inflamed, irritated anorectal surface to help make bowel movements less painful

Warnings

For external use only and/or intrarectal use only

Ask a doctor before use if you have

- heart disease
- high blood pressure
- thyroid disease
- diabetes
- trouble urinating due to an enlargement of the prostate gland

Ask a doctor or pharmacist before use if you are

presently taking a prescription drug for high blood pressure or depression.

When using this product

do not exceed the recommended daily dosage unless directed by a doctor.

Stop use and ask a doctor if

- bleeding occurs
- condition worsens or does not improve within 7 days
- introduction of applicator into the rectum causes additional pain

If pregnant or breast-feeding,

ask a health professional before use.

Keep out of reach of children.

If swallowed, get medical help or contact a Poison Control Center right away.

Directions

- adults: when practical, cleanse the affected area by patting or blotting with an appropriate cleansing wipe. Gently dry by patting or blotting with a tissue or a soft cloth before applying ointment.
- when first opening tube, puncture foil seal with top end of cap
- apply to the affected area up to 4 times daily, especially at night, in the morning or after each bowel movement
- intrarectal use: remove cover form applicator and attach tube, lubricate applicator well, then gently insert applicator into the rectum - thoroughly cleanse applicator after each use and replace cover
- also apply ointment to external area
- regular use provides continual therapy for relief of symptoms
- children under 12 years of age: ask a doctor

Other information

Store at 20o to 25oC (68o to 77oF)

Inactive ingredients

beeswax, benzoic acid, cetyl alcohol, blyerol, methylparaben, polyoxyethylene lauryl ether, propylparaben, stearyl alcohol

Active ingredients

Mineral oil 14%

Petrolatum 74.9%

Phenylephrine HCL 0.25%

Purpose

Protectant

Protectant

Vasoconstrictor

Questions or comments?

Call toll free: 1-800-883-0085

Package label

Best Choice Hemorrhoidal Ointment